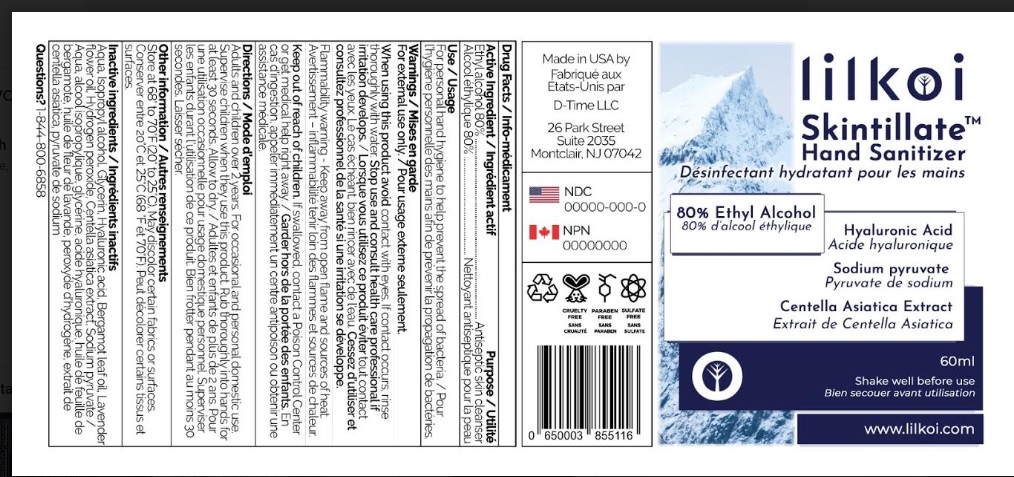 DRUG LABEL: Skintillate Hand Sanitizer
NDC: 75306-005 | Form: LIQUID
Manufacturer: D-Time Limited Liability Company
Category: otc | Type: HUMAN OTC DRUG LABEL
Date: 20211102

ACTIVE INGREDIENTS: ALCOHOL 80 mL/100 mL
INACTIVE INGREDIENTS: WATER; ISOPROPYL ALCOHOL; GLYCERIN; HYALURONIC ACID; BERGAMOT OIL; LAVENDER OIL; HYDROGEN PEROXIDE; CENTELLA ASIATICA; SODIUM PYRUVATE

Skintillate Hand Sanitizer

Active Ingredient

Alcohol 80% v/v.

Purpose

Antiseptic skin cleanser

Use

For personal hand hygiene to help prevent the spread of bacteria

Warning

For external use only
When using this product avoid contact with eyes.
Flammable. Keep away from heat and flame.

Ask doctor

Stop use and consult a healthcare professional if irritation develops.

Keep out of reach of children.

If swallowed, contact a Poison Control Center or , get medical help right away.

Directions

Adults and children over 2 years: ∙ For occasional and personal domestic use ∙ Supervise children when they use this product ∙ Spray onto hands and rub thoroughly for at least 30 seconds. Allow to dry.

Inactive ingredients

Water, Isopropyl alcohol, Glycerin, Hyaluronic Acid, Bergamot leaf oil, Lavender Flower, Hydrogen Peroxide, Centella Asiatica Extract, Sodium pyruvate

Other information

Store at 68 to 70 F (20 to 25 C). May discolor certain fabrics on surfaces

Questions?

1-844-800-6858